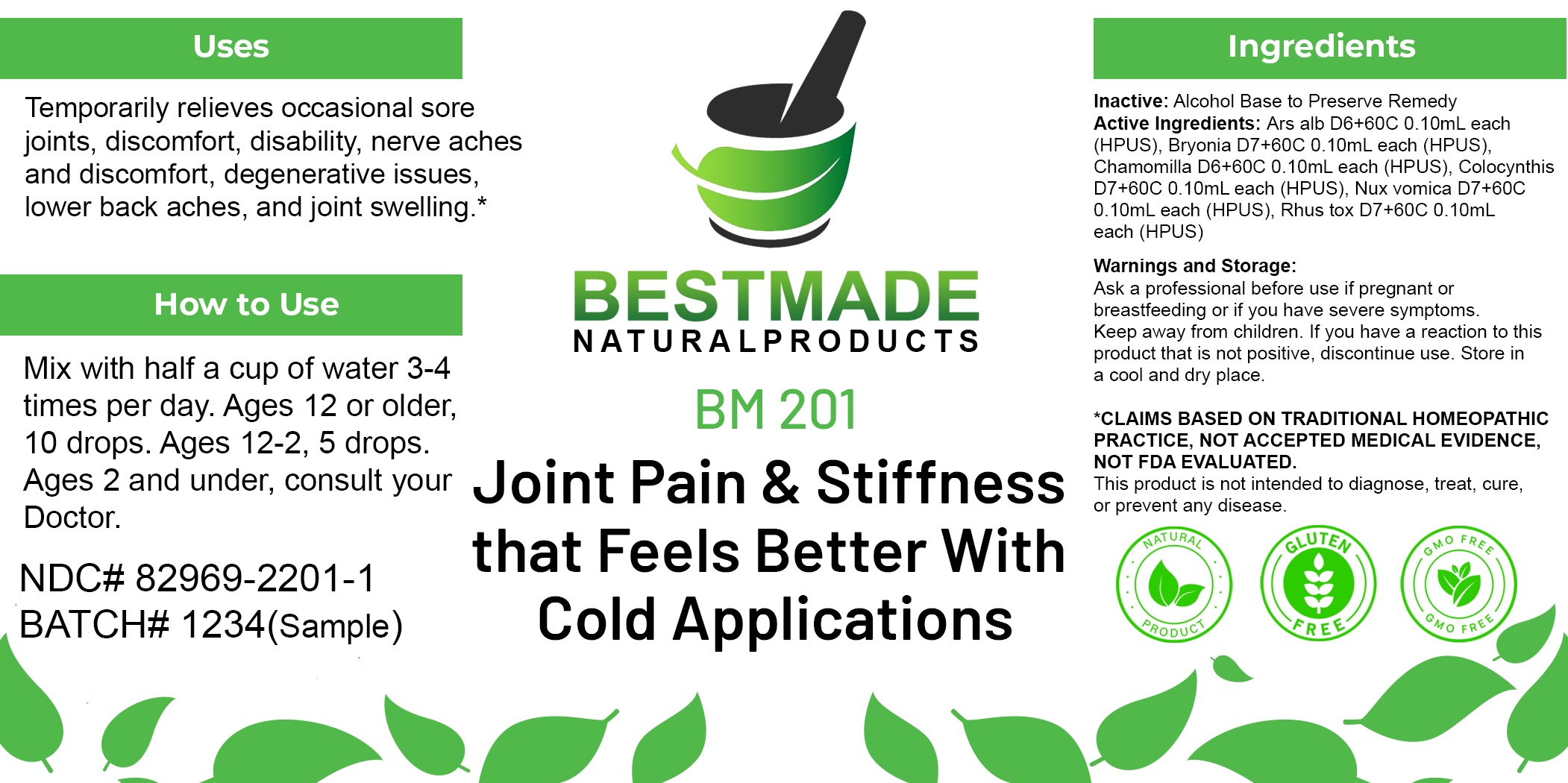 DRUG LABEL: Bestmade Natural Products BM201
NDC: 82969-2201 | Form: LIQUID
Manufacturer: Bestmade Natural Products
Category: homeopathic | Type: HUMAN OTC DRUG LABEL
Date: 20250225

ACTIVE INGREDIENTS: STRYCHNOS NUX-VOMICA SEED 30 [hp_C]/30 [hp_C]; ARSENIC TRIOXIDE 30 [hp_C]/30 [hp_C]; BRYONIA ALBA ROOT 30 [hp_C]/30 [hp_C]; MATRICARIA CHAMOMILLA 30 [hp_C]/30 [hp_C]; TOXICODENDRON PUBESCENS LEAF 30 [hp_C]/30 [hp_C]; CITRULLUS COLOCYNTHIS FRUIT PULP 30 [hp_C]/30 [hp_C]
INACTIVE INGREDIENTS: ALCOHOL 30 [hp_C]/30 [hp_C]

BM201

DOSAGE AND ADMINISTRATION

How to Use

Mix with half a cup of water 3-4 times per day. Ages 12 or older, 10 drops. Ages 12-2, 5 drops. Ages 2 and under, consult your Doctor.

Inactive:

Alcohol Base to Preserve Product

Active Ingredients:
Ars alb D6+60C 0.10mL each (HPUS), Bryonia D7+60C 0.10mL each (HPUS), Chamomilla D6+60C 0.10mL each (HPUS), Colocynthis D7+60C 0.10mL each (HPUS), Nux vomica D7+60C 0.10mL each (HPUS), Rhus tox D7+60C 0.10mL each (HPUS)

KEEP OUT OF REACH OF CHILDREN

Warnings and Storage:

Ask a professional before use if pregnant or breastfeeding or if you have severe symptoms.

Keep away from children. If you have a reaction to this product that is not positive, discontinue use. Store in a cool and dry place

*CLAIMS BASED ON TRADITIONAL HOMEOPATHIC PRACTICE, NOT ACCEPTED MEDICAL EVIDENCE NOT FDA EVALUATED.
This product is not intended to diagnose, treat, cure, or prevent any disease.

Warnings and Storage:

Ask a professional before use if pregnant or breastfeeding or if you have severe symptoms.

Keep away from children. If you have a reaction to this product that is not positive, discontinue use. Store in a cool and dry place

*CLAIMS BASED ON TRADITIONAL HOMEOPATHIC PRACTICE, NOT ACCEPTED MEDICAL EVIDENCE NOT FDA EVALUATED.
This product is not intended to diagnose, treat, cure, or prevent any disease.

Uses
Temporarily relieves occasional sore joints, discomfort, disability, nerve aches and discomfort, degenerative issues lower back aches, and joint swelling.*

Uses
Temporarily relieves occasional sore joints, discomfort, disability, nerve aches and discomfort, degenerative issues lower back aches, and joint swelling.*

Entire package label